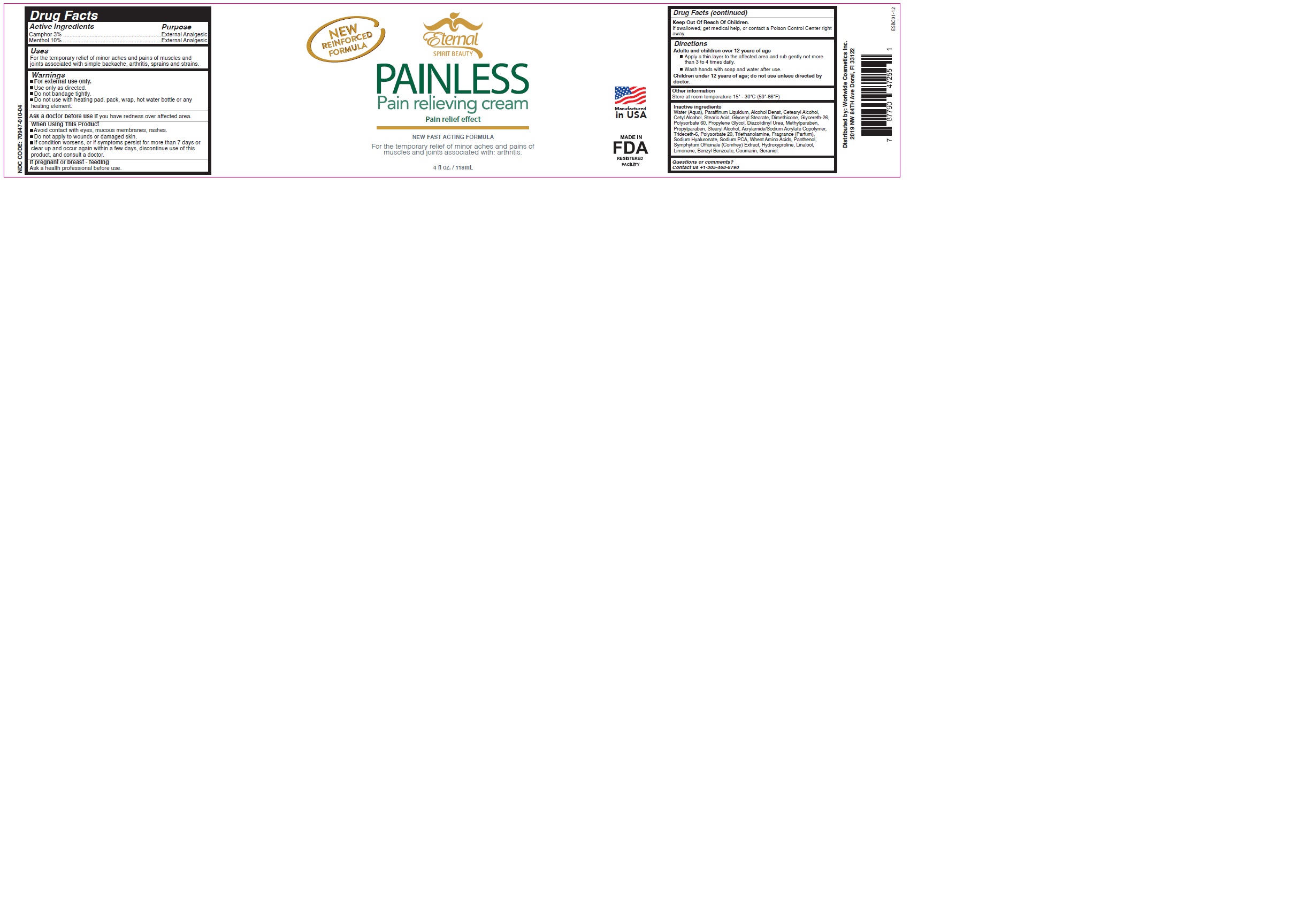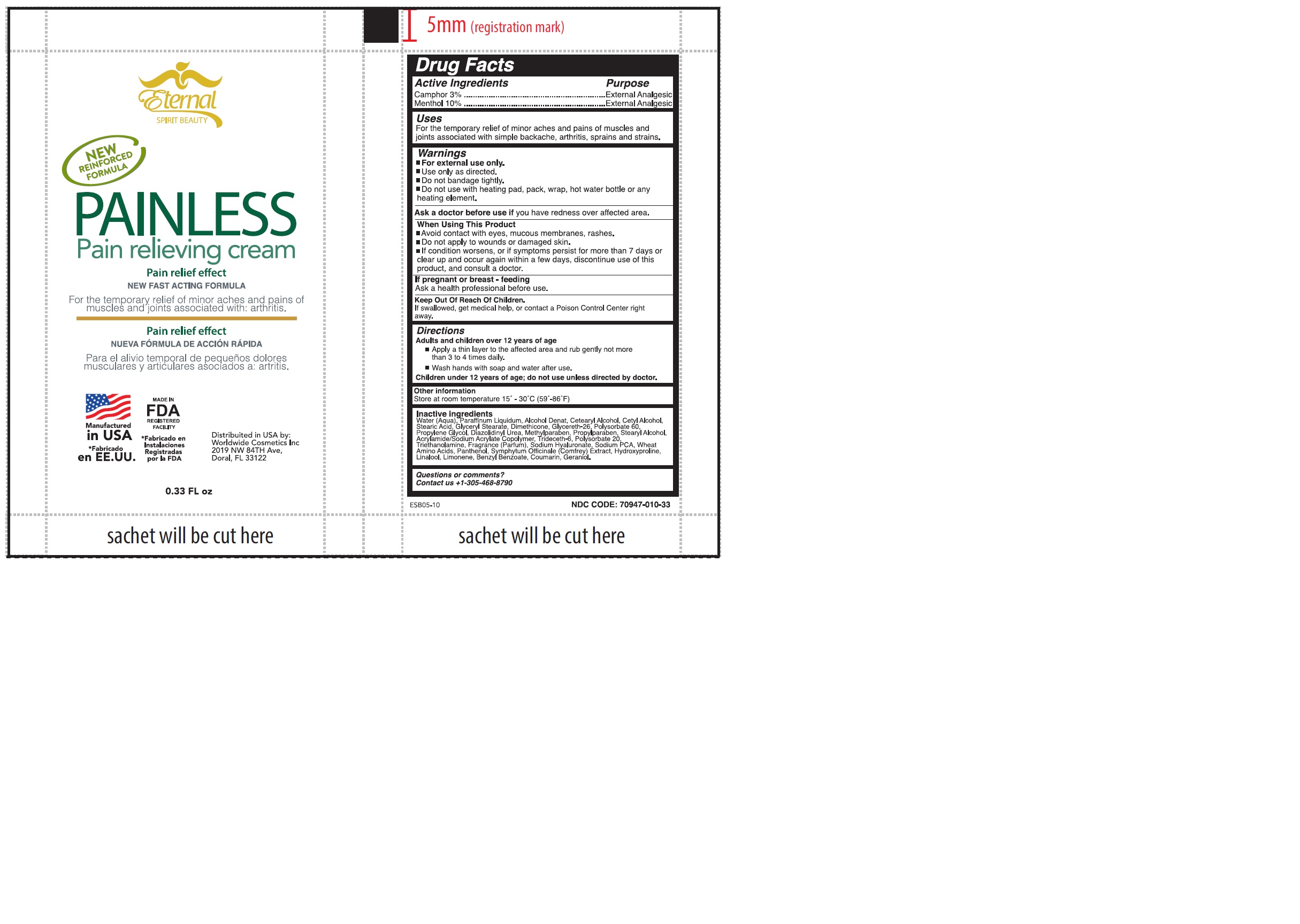 DRUG LABEL: ETERNAL SPIRIT BEAUTY PAINLESS
NDC: 70947-010 | Form: CREAM
Manufacturer: Worldwide Cosmetics, Inc
Category: otc | Type: HUMAN OTC DRUG LABEL
Date: 20241112

ACTIVE INGREDIENTS: MENTHOL, UNSPECIFIED FORM 10 g/100 g; CAMPHOR (NATURAL) 3 g/100 g
INACTIVE INGREDIENTS: LINALOOL, (+/-)-; POLYSORBATE 60; TROLAMINE; MINERAL OIL; GLYCERYL STEARATE SE; ACRYLIC ACID/SODIUM ACRYLATE COPOLYMER (1:1; 600 MPA.S AT 0.2%); AMINO ACIDS, WHEAT; PANTHENOL; ALCOHOL; STEARIC ACID; CETOSTEARYL ALCOHOL; CETYL ALCOHOL; DIMETHICONE; GLYCERETH-26; PROPYLENE GLYCOL; DIAZOLIDINYL UREA; METHYLPARABEN; PROPYLPARABEN; SYMPHYTUM OFFICINALE WHOLE; HYDROXYPROLINE; STEARYL ALCOHOL; TRIDECETH-6; HYALURONATE SODIUM; SODIUM PYRROLIDONE CARBOXYLATE; BENZYL BENZOATE; POLYSORBATE 20; WATER; GERANIOL; COUMARIN; LIMONENE, (+)-

70947-010-04
70947-010-33

ACTIVE INGREDIENT

Camphor 3%

Menthol 10%

PURPOSE

External Analgesic

USES:

For the temporary relief of minor aches and pains of muscles and joints
associated with simple backache, arthritis, sprains and strains

WARNINGS

•For external use only.

•Use only as directed.
•Do not bandage tightly.
•Do not use with heating pad, pack, wrap, hot water bottle or any heating element.

Ask a doctor before use if you have redness over affected area

WHEN USING

Avoid contact with eyes, mucous membranes, rashes.
Do not apply to wounds or damaged skin.
If condition worsens, or if symptoms persist for more than 7 days or clear up and occur again within a few days, discontinue use of this product, and consult a doctor.

If pregnant or breast – feeding

Ask a health professional before use.

KEEP OUT OF REACH OF CHILDREN

If swallowed, get medical help, or contact a Poison Control Center right away.

DIRECTIONS:

Adults and children over 12 years of age

apply a thin layer to the affected area and rub gently not more than 3 to 4 times daily.
Wash hands with soap and water after use.

Children under 12 years of age; do not use unless directed by doctor.

OTHER INFORMATION:

Store at room temperature 15º - 30ºC (59º - 86º F)

INACTIVE INGREDIENT

Water (Aqua), Paraffinum Liquidum, Alcohol Denat, Cetearyl Alcohol, Cetyl Alcohol, Stearic Acid, Glyceryl Stearate, Dimethicone, Glycereth-26, Polysorbate 60, Propylene Glycol, Diazolidinyl Urea, Methylparaben, Propylparaben, Stearyl Alcohol, Acrylamide/Sodium Acrylate Copolymer, Trideceth-6, Polysorbate 20, Triethanolamine, Fragrance (Parfum), Sodium Hyaluronate, Sodium PCA, Wheat Amino Acids, Panthenol, Symphytum Officinale (Comfrey) Extract, Hydroxyproline, Linalool, Limonene, Benzyl Benzoate, Coumarin, Geraniol.

QUESTIONS OR COMMENTS?

Contact us +1-305-468-8720